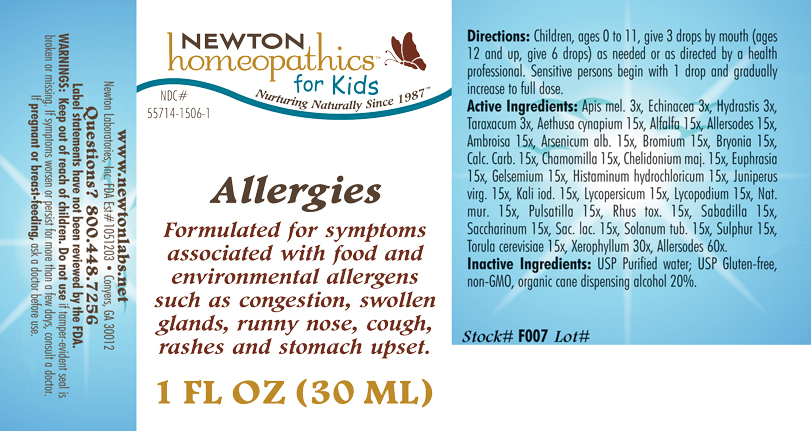 DRUG LABEL: Allergies 
NDC: 55714-1506 | Form: LIQUID
Manufacturer: Newton Laboratories, Inc.
Category: homeopathic | Type: HUMAN OTC DRUG LABEL
Date: 20110301

ACTIVE INGREDIENTS: Cow Milk 60 [hp_X]/1 mL; Skim Milk 60 [hp_X]/1 mL; Cow Milk Fat 60 [hp_X]/1 mL; Casein, Lactococcus Lactis Cultured, Aged 60 [hp_X]/1 mL; Casein, Lactococcus Lactis Cultured, Penicillium Roqueforti Cultured, Aged 60 [hp_X]/1 mL; Casein, Lactococcus Lactis Cultured, Penicillium Camemberti Cultured, Aged 60 [hp_X]/1 mL; Egg 60 [hp_X]/1 mL; Felis Catus Skin 60 [hp_X]/1 mL; Oryctolagus Cuniculus Skin 60 [hp_X]/1 mL; Equus Caballus Skin 60 [hp_X]/1 mL; Serinus Canaria Feather 60 [hp_X]/1 mL; Gallus Gallus Feather 60 [hp_X]/1 mL; Anas Platyrhynchos Feather 60 [hp_X]/1 mL; Anser Anser Feather 60 [hp_X]/1 mL; Melopsittacus Undulatus Feather 60 [hp_X]/1 mL; Phasianus Colchicus Feather 60 [hp_X]/1 mL; Meleagris Gallopavo Feather 60 [hp_X]/1 mL; Felis Catus Hair 60 [hp_X]/1 mL; Human Dander 60 [hp_X]/1 mL; Canis Lupus Familiaris Hair 60 [hp_X]/1 mL; Equus Caballus Hair 60 [hp_X]/1 mL; Oryctolagus Cuniculus Hair 60 [hp_X]/1 mL; Human Hair 60 [hp_X]/1 mL; Human Skin 60 [hp_X]/1 mL; Sheep Wool 60 [hp_X]/1 mL; Bos Taurus Hair 60 [hp_X]/1 mL; Capra Hircus Hair 60 [hp_X]/1 mL; Cavia Porcellus Hair 60 [hp_X]/1 mL; Mesocricetus Auratus Hair 60 [hp_X]/1 mL; Fd&c Yellow No. 5 60 [hp_X]/1 mL; D&c Yellow No. 10 60 [hp_X]/1 mL; Fd&c Yellow No. 6 60 [hp_X]/1 mL; Carmoisine 60 [hp_X]/1 mL; Amaranth 60 [hp_X]/1 mL; Ponceau 4r 60 [hp_X]/1 mL; Fd&c Red No. 3 60 [hp_X]/1 mL; Acid Red 1 60 [hp_X]/1 mL; Fd&c Blue No. 2 60 [hp_X]/1 mL; Sodium Copper Chlorophyllin 60 [hp_X]/1 mL; Acid Green 50 60 [hp_X]/1 mL; Sodium Benzoate 60 [hp_X]/1 mL; Potassium Benzoate 60 [hp_X]/1 mL; Propylparaben 60 [hp_X]/1 mL; Sodium Dithionate 60 [hp_X]/1 mL; 2-phenylphenol 60 [hp_X]/1 mL; Sodium Nitrite 60 [hp_X]/1 mL; Ascorbic Acid 60 [hp_X]/1 mL; Sodium Tripolyphosphate 60 [hp_X]/1 mL; Aspartame 60 [hp_X]/1 mL; Monosodium Glutamate 60 [hp_X]/1 mL; Barley 60 [hp_X]/1 mL; Corn 60 [hp_X]/1 mL; Wheat Gluten 60 [hp_X]/1 mL; Oat 60 [hp_X]/1 mL; White Rice 60 [hp_X]/1 mL; Rye 60 [hp_X]/1 mL; Wheat 60 [hp_X]/1 mL; Beef 60 [hp_X]/1 mL; Pork 60 [hp_X]/1 mL; Lamb 60 [hp_X]/1 mL; Chicken 60 [hp_X]/1 mL; Turkey 60 [hp_X]/1 mL; Quahog, Unspecified 60 [hp_X]/1 mL; Crab Leg, Unspecified 60 [hp_X]/1 mL; Oyster, Unspecified 60 [hp_X]/1 mL; Shrimp, Unspecified 60 [hp_X]/1 mL; Scallop, Unspecified 60 [hp_X]/1 mL; Xerophyllum Asphodeloides 30 [hp_X]/1 mL; Aethusa Cynapium 15 [hp_X]/1 mL; Alfalfa 15 [hp_X]/1 mL; Aletris Farinosa Root 15 [hp_X]/1 mL; Artemisia Vulgaris Root 15 [hp_X]/1 mL; Bellis Perennis 15 [hp_X]/1 mL; Dysphania Ambrosioides 15 [hp_X]/1 mL; Lycopus Virginicus 15 [hp_X]/1 mL; Phytolacca Americana Root 15 [hp_X]/1 mL; Populus Tremuloides Leaf 15 [hp_X]/1 mL; Populus Tremuloides Bark 15 [hp_X]/1 mL; Ptelea Trifoliata Bark 15 [hp_X]/1 mL; Sambucus Nigra Flowering Top 15 [hp_X]/1 mL; Trillium Erectum Root 15 [hp_X]/1 mL; Elymus Repens Root 15 [hp_X]/1 mL; Urtica Urens 15 [hp_X]/1 mL; Wyethia Helenioides Root 15 [hp_X]/1 mL; Yucca Filamentosa 15 [hp_X]/1 mL; Aconitum Napellus 15 [hp_X]/1 mL; Arundo Pliniana Root 15 [hp_X]/1 mL; Helianthemum Canadense 15 [hp_X]/1 mL; Drosera Rotundifolia 15 [hp_X]/1 mL; Solanum Dulcamara Top 15 [hp_X]/1 mL; Ledum Palustre Twig 15 [hp_X]/1 mL; Onosmodium Virginianum Whole 15 [hp_X]/1 mL; Pulsatilla Vulgaris 15 [hp_X]/1 mL; Sanguinaria Canadensis Root 15 [hp_X]/1 mL; Datura Stramonium 15 [hp_X]/1 mL; Atropa Belladonna 15 [hp_X]/1 mL; Capsicum 15 [hp_X]/1 mL; Hyoscyamus Niger 15 [hp_X]/1 mL; Solanum Nigrum Whole 15 [hp_X]/1 mL; Tobacco Leaf 15 [hp_X]/1 mL; Amanita Muscaria Fruiting Body 15 [hp_X]/1 mL; Onion 15 [hp_X]/1 mL; Garlic 15 [hp_X]/1 mL; Anacardium Occidentale Fruit 15 [hp_X]/1 mL; Lycoperdon Utriforme Fruiting Body 15 [hp_X]/1 mL; Caffeine 15 [hp_X]/1 mL; Cinnamon 15 [hp_X]/1 mL; Cynara Scolymus Leaf 15 [hp_X]/1 mL; Alpine Strawberry 15 [hp_X]/1 mL; Abrus Precatorius Seed 15 [hp_X]/1 mL; Glycyrrhiza Glabra 15 [hp_X]/1 mL; Mentha Piperita 15 [hp_X]/1 mL; Nutmeg 15 [hp_X]/1 mL; Lactose 15 [hp_X]/1 mL; Sucrose 15 [hp_X]/1 mL; Black Mustard Seed 15 [hp_X]/1 mL; Allylthiourea 15 [hp_X]/1 mL; Ustilago Maydis 15 [hp_X]/1 mL; Ginger 15 [hp_X]/1 mL; Aspergillus Niger Var. Niger 15 [hp_X]/1 mL; Cladosporium Herbarum 15 [hp_X]/1 mL; Brazil Nut 15 [hp_X]/1 mL; Hazelnut, Unspecified 15 [hp_X]/1 mL; Peanut 15 [hp_X]/1 mL; English Walnut 15 [hp_X]/1 mL; Trout, Unspecified 15 [hp_X]/1 mL; Cod, Unspecified 15 [hp_X]/1 mL; Haddock 15 [hp_X]/1 mL; Tuna, Unspecified 15 [hp_X]/1 mL; Salmon, Unspecified 15 [hp_X]/1 mL; Herring, Unspecified 15 [hp_X]/1 mL; Avena Sativa Pollen 15 [hp_X]/1 mL; Cynosurus Cristatus Pollen 15 [hp_X]/1 mL; Echinochloa Crus-galli Pollen 15 [hp_X]/1 mL; Poa Pratensis Pollen 15 [hp_X]/1 mL; Anthoxanthum Odoratum Pollen 15 [hp_X]/1 mL; Agrostis Gigantea Pollen 15 [hp_X]/1 mL; Bromus Secalinus Pollen 15 [hp_X]/1 mL; Phleum Pratense Pollen 15 [hp_X]/1 mL; Festuca Pratensis Pollen 15 [hp_X]/1 mL; Holcus Lanatus Pollen 15 [hp_X]/1 mL; Lolium Perenne Pollen 15 [hp_X]/1 mL; Fagus Sylvatica Pollen 15 [hp_X]/1 mL; Betula Pendula Pollen 15 [hp_X]/1 mL; Quercus Alba Pollen 15 [hp_X]/1 mL; Fraxinus Excelsior Pollen 15 [hp_X]/1 mL; Corylus Americana Pollen 15 [hp_X]/1 mL; Populus Nigra Pollen 15 [hp_X]/1 mL; Platanus Orientalis Pollen 15 [hp_X]/1 mL; Ulmus Glabra Pollen 15 [hp_X]/1 mL; Salix Alba Pollen 15 [hp_X]/1 mL; Narcissus Pseudonarcissus 15 [hp_X]/1 mL; Rosa Canina Flower 15 [hp_X]/1 mL; Lilium Candidum Flower 15 [hp_X]/1 mL; Dianthus Caryophyllus Flower 15 [hp_X]/1 mL; Ulex Europaeus Flower 15 [hp_X]/1 mL; Cytisus Scoparius Pollen 15 [hp_X]/1 mL; Calluna Vulgaris Pollen 15 [hp_X]/1 mL; Crataegus Monogyna Pollen 15 [hp_X]/1 mL; House Dust 15 [hp_X]/1 mL; Ambrosia Artemisiifolia 15 [hp_X]/1 mL; Arsenic Trioxide 15 [hp_X]/1 mL; Bromine 15 [hp_X]/1 mL; Bryonia Alba Root 15 [hp_X]/1 mL; Oyster Shell Calcium Carbonate, Crude 15 [hp_X]/1 mL; Matricaria Recutita 15 [hp_X]/1 mL; Chelidonium Majus 15 [hp_X]/1 mL; Euphrasia Stricta 15 [hp_X]/1 mL; Gelsemium Sempervirens Root 15 [hp_X]/1 mL; Histamine Dihydrochloride 15 [hp_X]/1 mL; Juniperus Virginiana Twig 15 [hp_X]/1 mL; Potassium Iodide 15 [hp_X]/1 mL; Solanum Lycopersicum 15 [hp_X]/1 mL; Lycopodium Clavatum Spore 15 [hp_X]/1 mL; Sodium Chloride 15 [hp_X]/1 mL; Toxicodendron Pubescens Leaf 15 [hp_X]/1 mL; Schoenocaulon Officinale Seed 15 [hp_X]/1 mL; Saccharin 15 [hp_X]/1 mL; Solanum Tuberosum 15 [hp_X]/1 mL; Sulfur 15 [hp_X]/1 mL; Saccharomyces Cerevisiae 15 [hp_X]/1 mL; Apis Mellifera 3 [hp_X]/1 mL; Echinacea, Unspecified 3 [hp_X]/1 mL; Goldenseal 3 [hp_X]/1 mL; Taraxacum Officinale 3 [hp_X]/1 mL; Alopecurus Pratensis Pollen 15 [hp_X]/1 mL; Primula Vulgaris 15 [hp_X]/1 mL
INACTIVE INGREDIENTS: Alcohol; Water

Allergies

INDICATIONS & USAGE SECTION

Allergies Formulated for symptoms associated with food and environmental allergens such as congestion, swollen glands, runny nose, cough, rashes and stomach upset.

DOSAGE & ADMINISTRATION SECTION

Directions: Children, ages 0 to 11, give 3 drops by mouth (ages 12 and up, give 6 drops) as needed or as directed by a health professional. Sensitive persons begin with 1 drop and gradually increase to full dose.

OTC - ACTIVE INGREDIENT SECTION

Allersodes 60x, Xerophyllum asphodeloides 30x, Aethusa cynapium 15x, Alfalfa 15x, Allersodes 15x, Ambrosia artemisiaefolia 15x, Arsenicum alb. 15x, Bromium 15x, Bryonia 15x, Calc. Carb. 15x, Chamomilla 15x, Chelidonium majus 15x, Euphrasia 15x, Gelsemium 15x, Histaminum hydrochloricum 15x, Juniperus virginiana 15x, Kali iod. 15x, Lycopersicum esculentum 15x, Lycopodium 15x, Nat. mur. 15x, Pulsatilla 15x, Rhus toxicodendron 15x, Sabadilla 15x, Saccharinum 15x, Sac lac. 15x, Solanum tuberosum 15x, Sulphur 15x, Torula cerevisiae 15x, Apis mel. 3x, Echinacea 3x, Hydrastis 3x, Taraxacum 3x.

OTC - PURPOSE SECTION

Formulated for symptoms associated with food and environmental allergens such as congestion, swollen glands, runny nose, cough, rashes and stomach upset.

INACTIVE INGREDIENT SECTION

Inactive Ingredients: USP Purified Water; USP Gluten-free, non-GMO, organic cane dispensing alcohol 20%.

QUESTIONS SECTION

www.newtonlabs.net Newton Laboratories, Inc. FDA Est # 1051203 - Conyers, GA 30012
Questions? 1.800.448.7256

WARNINGS SECTION

Warning: Keep out of reach of children. Do not use if tamper-evident seal is broken or missing. If symptoms worsen or persist for more than a few days, consult a doctor. If pregnant or breast-feeding, ask a doctor before use.

OTC - PREGNANCY OR BREAST FEEDING SECTION

If pregnant or breast-feeding, ask a doctor before use.

OTC - KEEP OUT OF REACH OF CHILDREN SECTION

Keep out of reach of children.